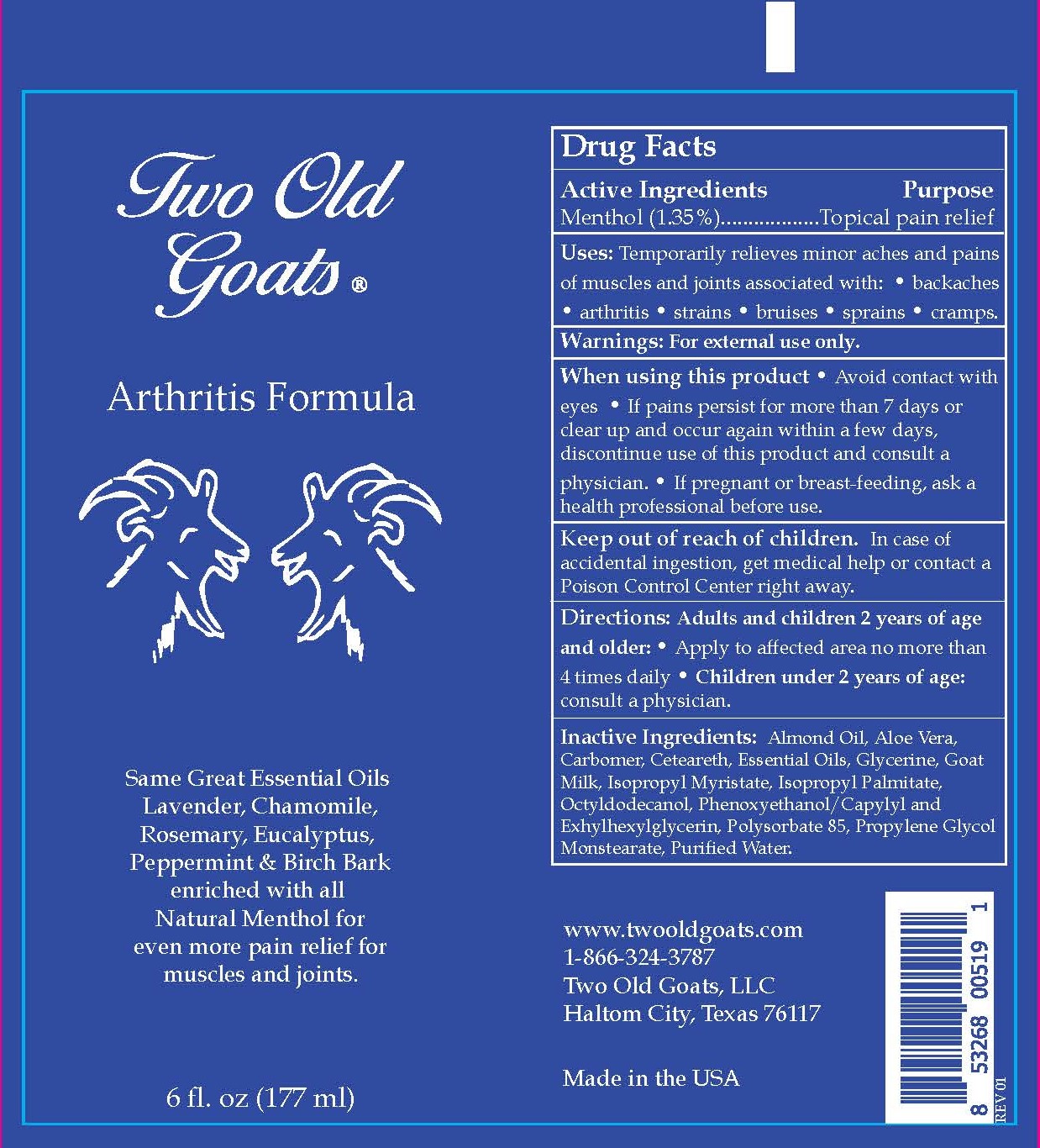 DRUG LABEL: Two Old Goats Arthritis Formula
NDC: 73316-100 | Form: LOTION
Manufacturer: Two Old Goats
Category: otc | Type: HUMAN OTC DRUG LABEL
Date: 20210824

ACTIVE INGREDIENTS: MENTHOL 1.35 mg/100 mL
INACTIVE INGREDIENTS: POLYSORBATE 85; LAVENDER OIL; CETEARETH-12; ISOPROPYL PALMITATE; ISOPROPYL MYRISTATE; PROPYLENE GLYCOL MONOSTEARATE; GLYCERYL STEARATE SE; MINERAL OIL; PHENOXYETHANOL; CAPRYLYL GLYCOL; BETULA PENDULA BARK; ROSEMARY OIL; CHAMOMILE; ALMOND OIL; ACRYLAMIDE; ETHYLHEXYLGLYCERIN; GOAT MILK; PEPPERMINT OIL; PEG-20 METHYL GLUCOSE SESQUISTEARATE; EUCALYPTUS GLOBULUS WHOLE; OCTYLDODECANOL; ALOE VERA LEAF; GLYCERIN; WATER

Two Old Goats Arthritus Formula

Distributed by: Two Old Goats, Haltom, Texas 76117

Active Ingredient(s)

Menthol 1.35%

Purpose

Temporarily relieves minor aches and pains of muscles and joints associated with: backaches, arthritis, strains, bruises, sprains and cramps

Use

Temporarily relieves minor pain associated with:

arthritis
simple backache
muscle strains
sprains
bruises
cramps

Warnings

For external use only. When using this product avoid contact with eyes.

Do not use

- in children less than 2 years of age consult a doctor

When using this product keep out of eyes, ears, and mouth. In case of contact with eyes, rinse eyes thoroughly with water.
Stop use and ask a doctor if irritation or rash occurs. These may be signs of a serious condition.
Keep out of reach of children. If swallowed, get medical help or contact a Poison Control Center right away.

Stop use and ask a doctor if irritation or rash occurs. These may be signs of a serious condition.

Keep out of reach of children. If swallowed, get medical help or contact a Poison Control Center right away.

Directions

- Adults and children 2 years of age and older: Apply to affected area not more than 4 times daily
- Children under 2 years of age: Consulkt a doctor.

Other information

- Store between 15-30C (59-86F)
- Avoid freezing and excessive heat above 40C (104F)

Inactive ingredients

glycerin, Purified Water Carbomer, aloe Vera,Glycerine ,Propylene glycol Monstearate,Isopropyl Palmitate, Isopropyl Myristat,

Octyldodecanol, Glyceryl Stearate Ceteareth-12, PEG 20 Methyl Glucose Sesquistearate, Phenoxyethanol /Caprylyl Glycol, Ethylhexylglycerin, Goat Milk, Menthol, Lavender, Birch Bark, Rosemary, Peppermint, Eucalyptus, Chamomile, Almond Oil, Acylamide Compolymer/Polysorbate 85

Package Label - Principal Display Panel

177 ml NDC: 73316-100-06